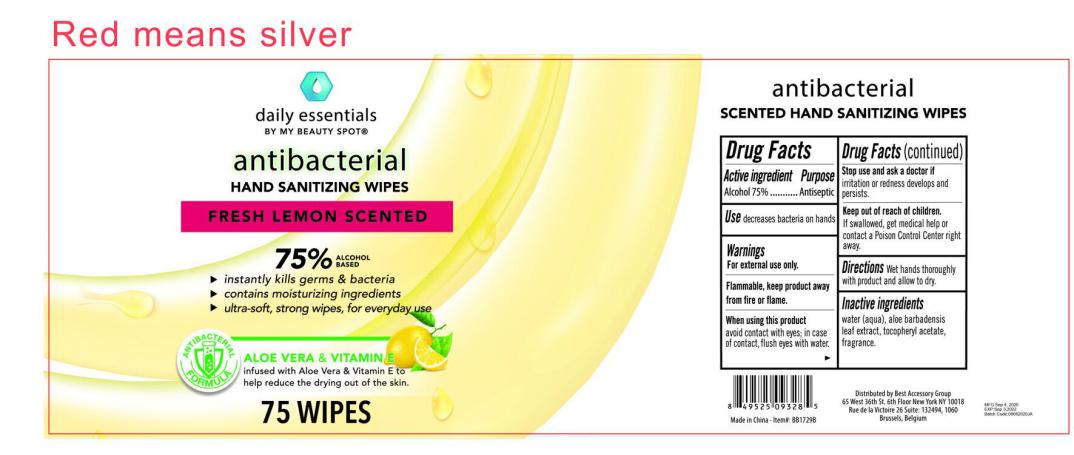 DRUG LABEL: BB1721B 75% ALCOHOL BASED ANTIBACTERIAL HAND WIPES FRESH LEMON SCENTED
NDC: 78936-012 | Form: SWAB
Manufacturer: Hangzhou Caring Cleaning Commodity Co.,Ltd
Category: otc | Type: HUMAN OTC DRUG LABEL
Date: 20200904

ACTIVE INGREDIENTS: ALCOHOL 75 g/100 g
INACTIVE INGREDIENTS: ALOE VERA LEAF; ALPHA-TOCOPHEROL ACETATE; WATER; FRAGRANCE LEMON ORC2001060

BB1721B 75% ALCOHOL BASED ANTIBACTERIAL HAND WIPES FRESH LEMON SCENTED

Active Ingredient(s)

Alcohol 75%

Purpose

Antiseptic

Use

Decreases bacteria on hands

Warnings

For external use only.

Flammable, keep away from fire or flame.

When using this product

Avoid contact with eyes; in case of contact, flush eyes with water

Stop use and ask a doctor if irritation or redness develops and persists.

Keep out of reach of children. If swallowed, get medical help or contact a Poison Control Center right away.

Directions

Wet hands thoroughly with product and allow to dry

Inactive ingredients

Water,Aloe Barbadensis Leaf Extract,Tocopheryl Acetate,Fragrance

Package Label - Principal Display Panel

75 POUCH IN 1 PAIL NDC: 78936-012-02